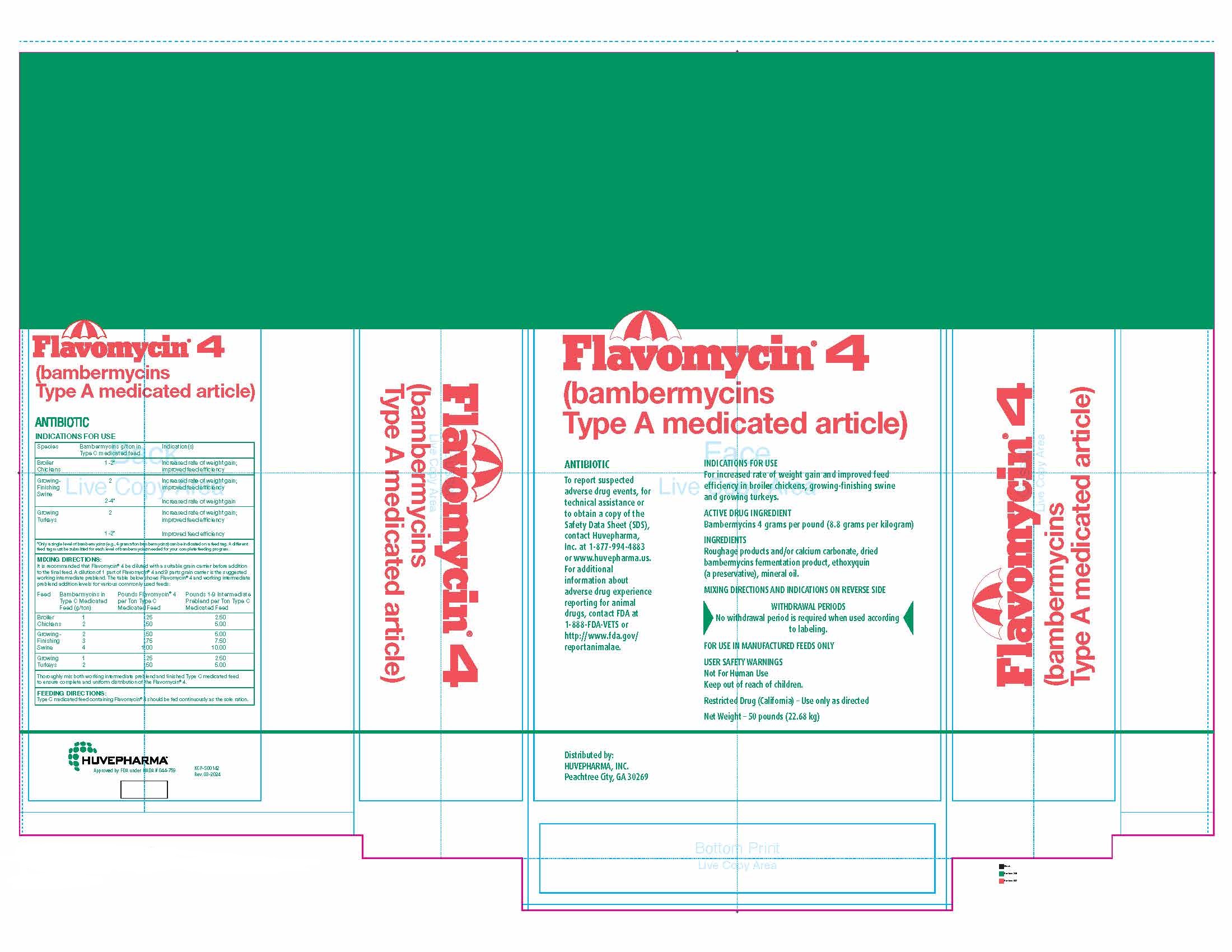 DRUG LABEL: Flavomycin
NDC: 23243-2060 | Form: POWDER
Manufacturer: Huvepharma, Inc.
Category: animal | Type: OTC TYPE A MEDICATED ARTICLE ANIMAL DRUG LABEL
Date: 20240501

ACTIVE INGREDIENTS: BAMBERMYCINS 8.8 g/1 kg
INACTIVE INGREDIENTS: MINERAL OIL; CALCIUM CARBONATE

FLAVOMYCIN® 4
(bambermycins Type A medicated article)

ADVERSE REACTIONS

ANTIBIOTIC

To report suspected adverse drug events, for technical assistance or
to obtain a copy of the Safety Data Sheet (SDS), contact Huvepharma,
Inc. at 1-877-994-4883 or www.huvepharma.us. For additional information
about adverse drug experience reporting for animal drugs, contact FDA at
1-888-FDA-VETS or http://www.fda.gov/reportanimalae.

INDICATIONS FOR USE

For increased rate of weight gain and improved feed efficiency in broiler chickens,
growing-finishing swine and growing turkeys.

ACTIVE DRUG INGREDIENT

Bambermycins 4 grams per pound (8.8 grams per kilogram)

INACTIVE INGREDIENT

INGREDIENTS

Roughage products and/or calcium carbonate, dried bambermycins fermentation product,
ethoxyquin (a preservative), mineral oil.

MIXING DIRECTIONS AND INDICATIONS ON REVERSE SIDE

RESIDUE WARNING

WITHDRAWAL PERIODS
No withdrawal period is required when used according to labeling.

USER SAFETY WARNINGS

FOR USE IN MANUFACTURED FEEDS ONLY

USER SAFETY WARNINGS
Not For Human Use
Keep out of reach of children.

Restricted Drug (California) – Use only as directed

Net Weight – 50 pounds (22.68 kg)

Distributed by:
HUVEPHARMA, INC.
Peachtree City, GA 30269

VETERINARY INDICATIONS

FLAVOMYCIN® 4
(bambermycins Type A Medicated Article)

ANTIBIOTIC

INDICATIONS FOR USE

Species |  | Bambermycins g/ton in; Type C medicated feed |  | Indication(s)
Broiler; Chickens |  | 1-2* |  | Increased rate of weight gain;; improved feed efficiency
Growing-; Finishing; Swine |  | 2 |  | Increased rate of weight gain;; improved feed efficiency
Growing-; Finishing; Swine |  | 2-4* |  | Increased rate of weight gain
Growing Turkeys |  | 2 |  | Increased rate of weight gain;; improved feed efficiency
Growing Turkeys |  | 1-2* |  | Improved feed efficiency
*Only a single level of bambermycins (e.g., 4 grams/ton bambermycins) can be indicated on a feed tag. A different feed tag must be submitted for each level of bambermycins needed for your complete feeding program.
MIXING DIRECTIONS:
It is recommended that Flavomycin® 4 be diluted with a suitable grain carrier before addition to the final feed. A dilution of 1 part of Flavomycin® 4 and 9 parts grain carrier is the suggested working intermediate preblend. The table below shows Flavomycin® 4 and working intermediate preblend addition levels for various commonly used feeds:
Feed | Bambermycins in Type C Medicated Feed (g/ton) |  | Pounds Flavomycin® 4 per Ton Type C Medicated Feed |  | Pounds 1-9 Intermediate; Preblend per Ton Type C Medicated Feed
Broiler; Chickens | 1; 2 |  | .25; .50 |  | 2.50; 5.00
Growing-; Finishing; Swine | 2; 3; 4 |  | .50; .75; 1.00 |  | 5.00; 7.50; 10.00
Growing; Turkeys | 1; 2 |  | .25; .50 |  | 2.50; 5.00
Thoroughly mix both working intermediate preblend and finished Type C medicated feed to ensure complete and uniform distribution of the Flavomycin® 4.
FEEDING DIRECTIONS:
Type C medicated feed containing Flavomycin® 4 should be fed continuously as the sole ration.

Huvepharma®

Approved by FDA under NADA #044-759